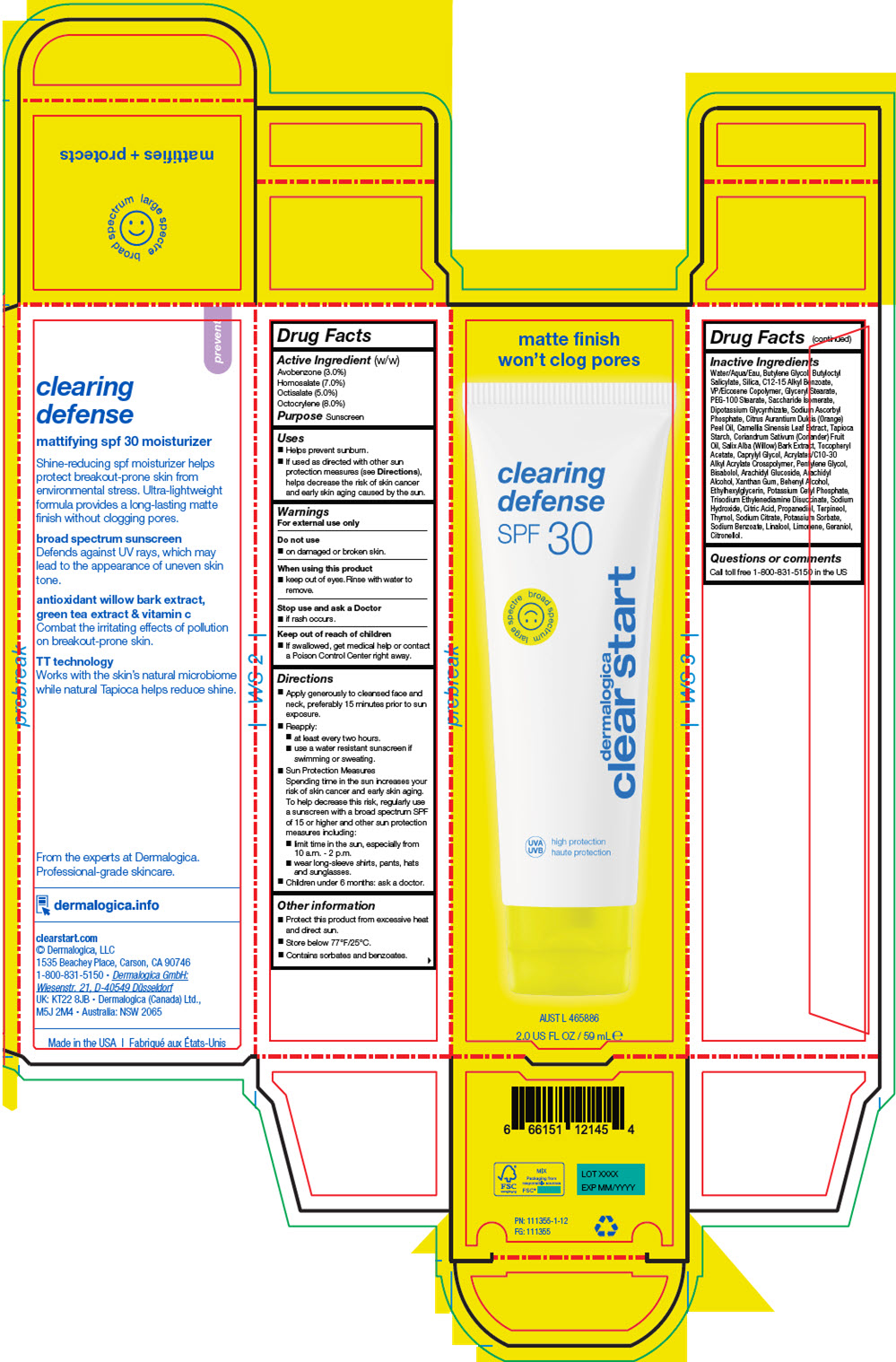 DRUG LABEL: CLEARING DEFENSE SPF30
NDC: 68479-872 | Form: LOTION
Manufacturer: Dermalogica, LLC.
Category: otc | Type: HUMAN OTC DRUG LABEL
Date: 20241127

ACTIVE INGREDIENTS: Octocrylene 8 mg/100 mL; Homosalate 7 mg/100 mL; Octisalate 5 mg/100 mL; Avobenzone 3 mg/100 mL
INACTIVE INGREDIENTS: Water; Butylene Glycol; Butyloctyl Salicylate; SILICON DIOXIDE; ALKYL (C12-15) BENZOATE; VINYLPYRROLIDONE/EICOSENE COPOLYMER; GLYCERYL MONOSTEARATE; PEG-100 Stearate; Saccharide Isomerate; Potassium Cetyl Phosphate; Pentylene Glycol; Arachidyl Alcohol; Propanediol; STARCH, TAPIOCA; Caprylyl Glycol; DOCOSANOL; LEVOMENOL; Xanthan Gum; ACRYLATES/C10-30 ALKYL ACRYLATE CROSSPOLYMER (60000 MPA.S); Arachidyl Glucoside; Ethylhexylglycerin; .ALPHA.-TOCOPHEROL ACETATE; GLYCYRRHIZINATE DIPOTASSIUM; Sodium Ascorbyl Phosphate; CORIANDER OIL; Trisodium Ethylenediamine Disuccinate; ORANGE OIL, COLD PRESSED; GREEN TEA LEAF; SALIX ALBA BARK; Terpineol; Thymol; Sodium Hydroxide; CITRIC ACID MONOHYDRATE; SODIUM CITRATE, UNSPECIFIED FORM; Potassium Sorbate; Sodium Benzoate

CLEARING DEFENSE SPF30

Drug Facts

Active Ingredient (w/w)

Avobenzone (3.0%)
Homosalate (7.0%)
Octisalate (5.0%)
Octocrylene (8.0%)

Purpose

Sunscreen

Uses

- Helps prevent sunburn.
- If used as directed with other sun protection measures (see Directions), helps decrease the risk of skin cancer and early skin aging caused by the sun.

Warnings

For external use only

Do not use

- on damaged or broken skin.

When using this product

- keep out of eyes. Rinse with water to remove.

Stop use and ask a Doctor

- if rash occurs.

Keep out of reach of children

- If swallowed, get medical help or contact a Poison Control Center right away.

Directions

- Apply generously to cleansed face and neck, preferably 15 minutes prior to sun exposure.
- Reapply:
  - at least every two hours.
  - use a water resistant sunscreen if swimming or sweating.
- Sun Protection Measures
  Spending time in the sun increases your risk of skin cancer and early skin aging. To help decrease this risk, regularly use a sunscreen with a broad spectrum SPF of 15 or higher and other sun protection measures including:
  - limit time in the sun, especially from 10 a.m. - 2 p.m.
  - wear long-sleeve shirts, pants, hats and sunglasses.
- Children under 6 months: ask a doctor.

Other information

- Protect this product from excessive heat and direct sun.
- Store below 77°F/25°C.
- Contains sorbates and benzoates.

Inactive Ingredients

Water/Aqua/Eau, Butylene Glycol, Butyloctyl Salicylate, Silica, C12-15 Alkyl Benzoate, VP/Eicosene Copolymer, Glyceryl Stearate, PEG-100 Stearate, Saccharide Isomerate, Dipotassium Glycyrrhizate, Sodium Ascorbyl Phosphate, Citrus Aurantium Dulcis (Orange) Peel Oil, Camellia Sinensis Leaf Extract, Tapioca Starch, Coriandrum Sativum (Coriander) Fruit Oil, Salix Alba (Willow) Bark Extract, Tocopheryl Acetate, Caprylyl Glycol, Acrylates/C10-30 Alkyl Acrylate Crosspolymer, Pentylene Glycol, Bisabolol, Arachidyl Glucoside, Arachidyl Alcohol, Xanthan Gum, Behenyl Alcohol, Ethylhexylglycerin, Potassium Cetyl Phosphate, Trisodium Ethylenediamine Disuccinate, Sodium Hydroxide, Citric Acid, Propanediol, Terpineol, Thymol, Sodium Citrate, Potassium Sorbate, Sodium Benzoate, Linalool, Limonene, Geraniol, Citronellol.

Questions or comments

Call toll free 1-800-831-5150 in the US

PRINCIPAL DISPLAY PANEL - 59 mL Tube Carton

matte finish
won't clog pores

clearing
defense
SPF 30

broad spectrum

dermalogica
clear start

UVA
UVB

high protection

AUST L 465886

2.0 US FL OZ / 59 mL e